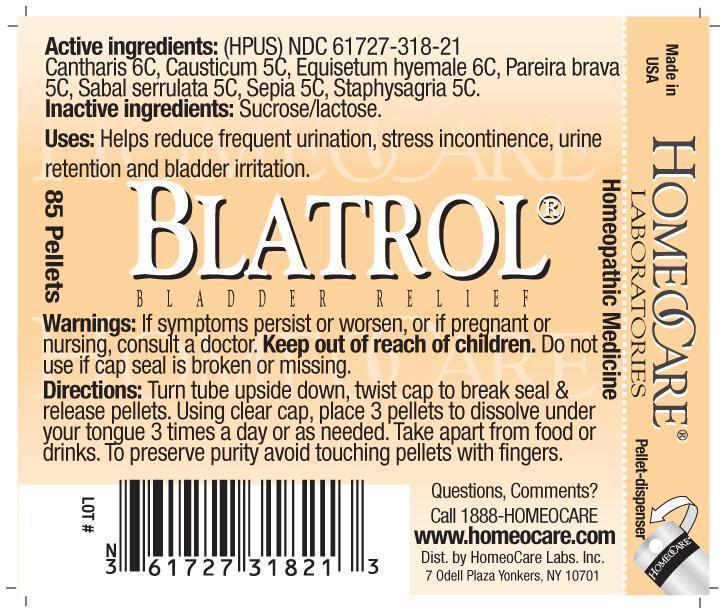 DRUG LABEL: Blatrol Bladder Relief
NDC: 61727-318 | Form: PELLET
Manufacturer: Homeocare Laboratories
Category: homeopathic | Type: HUMAN OTC DRUG LABEL
Date: 20181231

ACTIVE INGREDIENTS: LYTTA VESICATORIA 6 [hp_C]/4 g; CAUSTICUM 5 [hp_C]/4 g; EQUISETUM HYEMALE 6 [hp_C]/4 g; CHONDRODENDRON TOMENTOSUM ROOT 5 [hp_C]/4 g; SAW PALMETTO 5 [hp_C]/4 g; SEPIA OFFICINALIS JUICE 5 [hp_C]/4 g; DELPHINIUM STAPHISAGRIA SEED 5 [hp_C]/4 g
INACTIVE INGREDIENTS: SUCROSE; LACTOSE

Blatrol Bladder Relief

Active Ingredients:

Cantharis 6C, Causticum 5C, Equisetem hyemale 6C, Pareira brava 5C, Sabal serrulata 5C, Sepia 5C, Staphysagria 5C.

Inactive Ingredients:

Sucrose/lactose.

Purpose:

Helps reduce frequent urination, stress incontinence, urine retention and bladder irritation.

Indications & Usage:

Turn tube upside down, twist cap to break seal & release pellets. Using clear cap, place 3 pellets to dissolve under your tongue 3 times a day or as needed. Take apart from food or drinks. To preserve purity avoid touching pellets with fingers.

Warnings:

If symptoms persist or worsen, or if pregnant or nursing, consult a doctor. Keep out of reach of children. Do not use if cap seal is broken or missing.

Dosage & Administration:

Turn tube upside down, twist cap to break seal & release pellets. Using clear cap, place 3 pellets to dissolve under your tongue 3 times a day or as needed. Take apart from food or drinks. To preserve purity avoid touching pellets with fingers.

Keep out of reach of children.